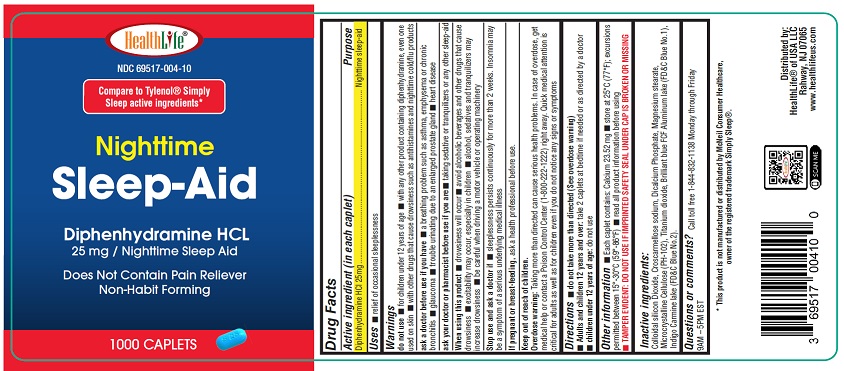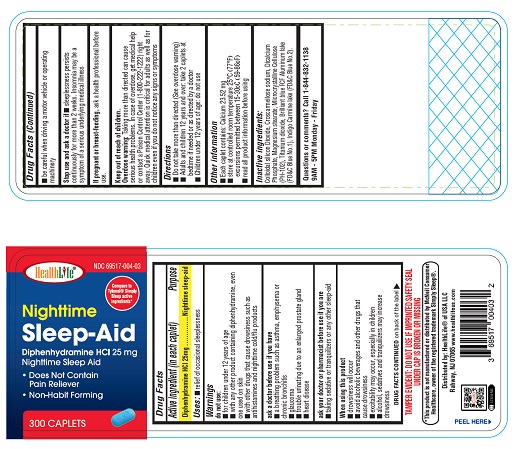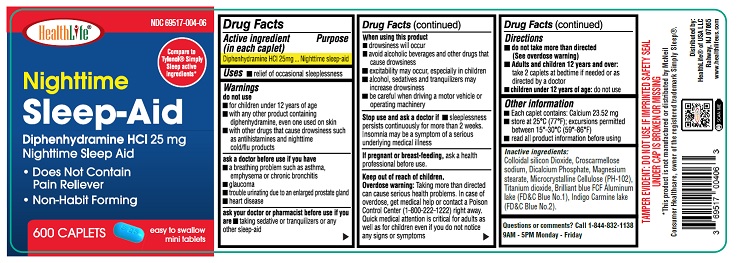 DRUG LABEL: Nighttime Sleep Aid
NDC: 69517-004 | Form: TABLET, COATED
Manufacturer: HealthLife of USA LLC
Category: otc | Type: HUMAN OTC DRUG LABEL
Date: 20250925

ACTIVE INGREDIENTS: DIPHENHYDRAMINE HYDROCHLORIDE 25 mg/1 1
INACTIVE INGREDIENTS: ANHYDROUS DIBASIC CALCIUM PHOSPHATE; MICROCRYSTALLINE CELLULOSE; CROSCARMELLOSE SODIUM; SILICON DIOXIDE; MAGNESIUM STEARATE; FD&C BLUE NO. 1; FD&C BLUE NO. 2; TITANIUM DIOXIDE

Active ingredient (in each caplet)

Diphenhydramine HCl 25 mg

Purpose

Nighttime sleep-aid

Uses:

- relief of occasional sleeplessness

Warnings

do not use:

- for children under 12 years of age
- with any other product containing diphenhydramine, even one used on skin
- with other drugs that cause drowsiness such as antihistamines and nighttime cold/flu products

ask a doctor before use if you have

- a breathing problem such as asthma, emphysema or chronic bronchitis
- glaucoma
- trouble urinating due to an enlarged prostate gland
- heart disease

ask your doctor or pharmacist before use if you are

- taking sedative or tranquilizers or any other sleep-aid

When using this product

- drowsiness will occur
- avoid alcoholic beverages and other drugs that cause drowsiness
- excitability may occur, especially in children
- alcohol, sedatives and tranquilizers may increase drowsiness
- be careful when driving a motor vehicle or operating machinery

Stop use and ask a doctor if

sleeplessness persists continuously for more than 2 weeks. Insomnia may be a symptom of a serious underlying medical illness

If pregnant or breast-feeding,

ask a health professional before use.

Keep out of reach of children.

Overdose warning: Taking more than directed can cause serious health problems. In case of overdose, get medical help or contact a Poison Control Center (1-800-222-1222) right away. Quick medical attention is critical for adults as well as for children even if you do not notice any signs or symptoms

Directions

- do not take more than directed(see overdose warning)
- adults and children 12 years of age and over:- take 2 caplets at bedtime if needed or as directed by a doctor
- children under 12 years of age:do not use

Other Information

- Each caplet contains: Calcium 23.52 mg
- store at controlled room temperature 25°C (77°F); excursions permitted between 15-30°C (59-86°F)
- read all product information before using

Inactive Ingredients

Colloidal Silicon Dioxide, Croscarmellose Sodium, Dicalcium Phosphate, Magnesium Stearate, Microcrystalline Cellulose (PH-102), Titanium dioxide, Brilliant Blue FCF Aluminum lack (FD&C Blue No. 1), Indico Carmel lake (FD&C Blue No. 2).

Questions or comments?

Call 1-844-832-1138

9AM – 5PM Monday - Friday